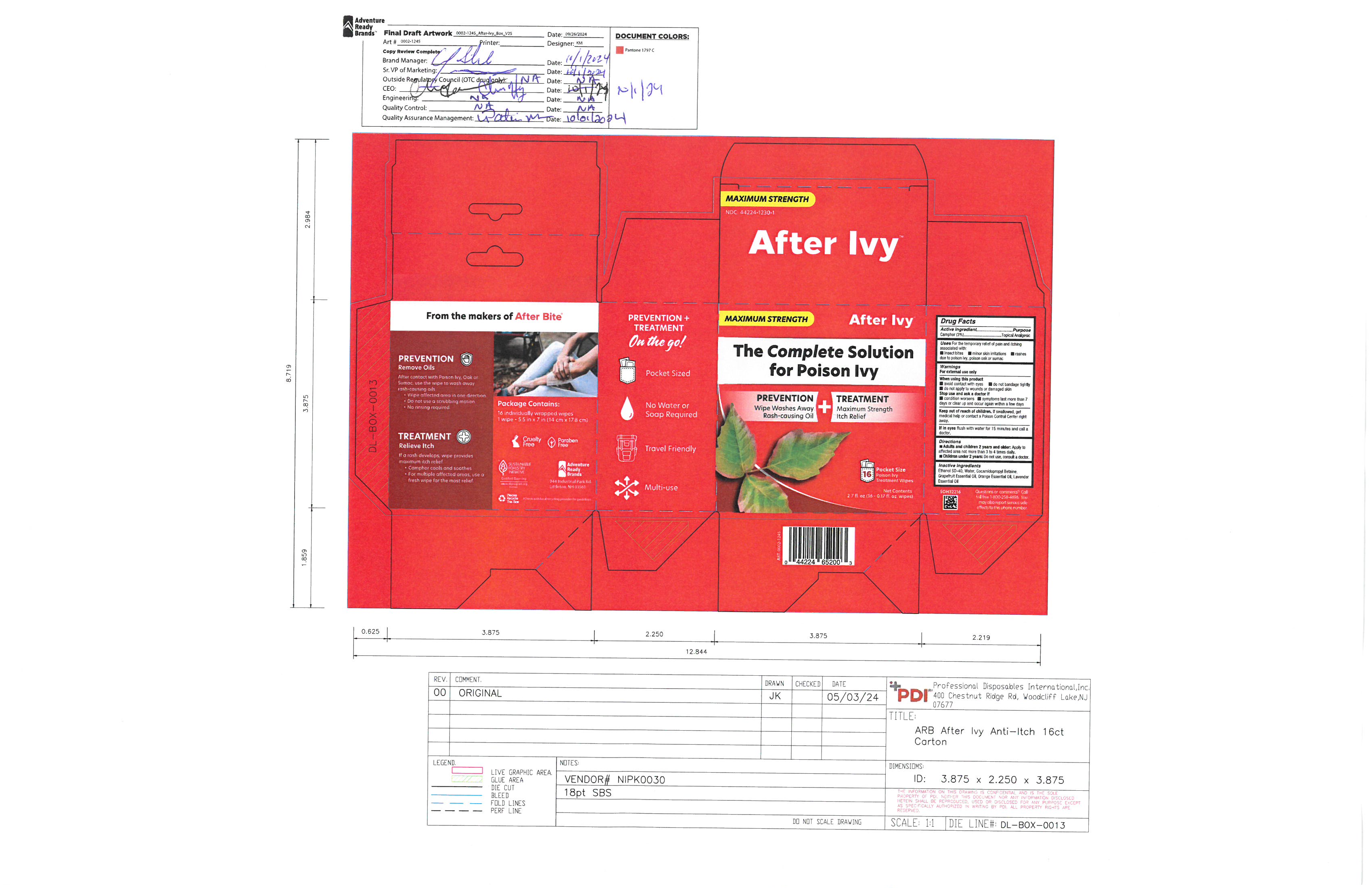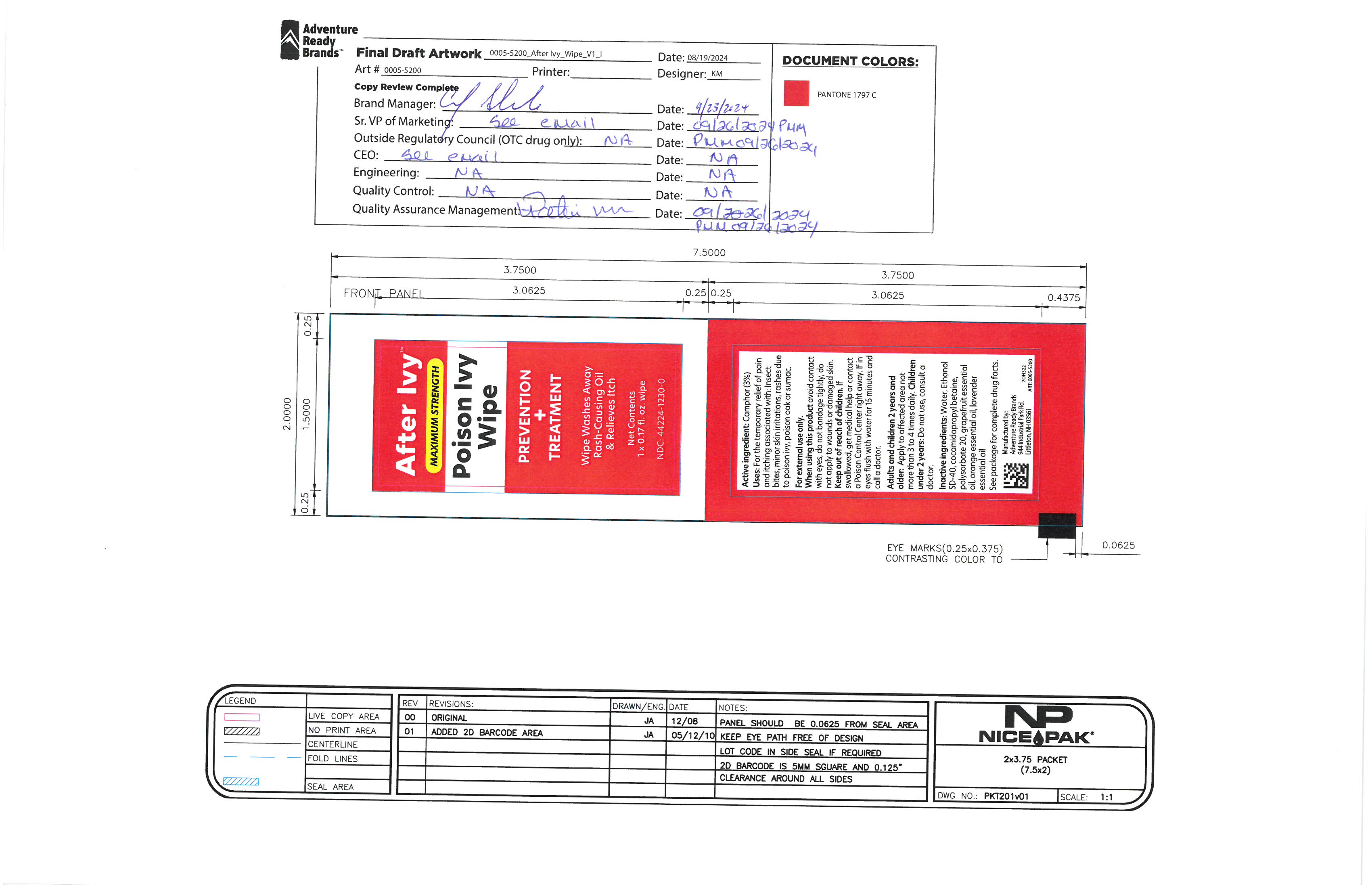 DRUG LABEL: After Ivy Wipe
NDC: 44224-1230 | Form: SOLUTION
Manufacturer: Tender Corporation d/b/a Adventure Ready Brands
Category: otc | Type: HUMAN OTC DRUG LABEL
Date: 20251117

ACTIVE INGREDIENTS: CAMPHOR (SYNTHETIC) 2.295 g/76.5 g
INACTIVE INGREDIENTS: LAVENDER OIL 0.38 g/76.5 g; GRAPEFRUIT OIL 0.57 g/76.5 g; COCAMIDOPROPYL BETAINE 1.5 g/76.5 g; WATER 11.48 g/76.5 g; ALCOHOL 59.67 g/76.5 g; BORAGE SEED OIL 0.57 g/76.5 g

After Ivy Wipe

ACTIVE INGREDIENT

Camphor- 3%

PURPOSE

For the temporary relief of pain and itching associated with: insect bites, minor skin irritations, rahses due to poison ivy, poison oak, or sumac.

When using this product avoid contact with eyes, do not bandage tightly, do not apply to wounds or damaged skin.

KEEP OUT OF REACH OF CHILDREN

If swallowed, get medical help or contact a poison control center right away. If in eyes, flush with water for fifteen minutes and calll a doctor.

WHEN USING

Apply to affected area not more than three to four times daily.

ASK DOCTOR

Children under two years do not use, consult a doctor.

DOSAGE AND ADMINISTRATION

0.15g Camphor

INACTIVE INGREDIENT

Water, Ethanol, Cocamidopropyl Betaine, Polysorbate 20, Grapefruit Essential Oil, Orange Essential Oil, Lavender Essential Oil

INDICATIONS AND USAGE

Temporary relief of pain and itching associated with insect bites, minor skin irritation, rashes due to poinson ivy, poison oak, sumac.